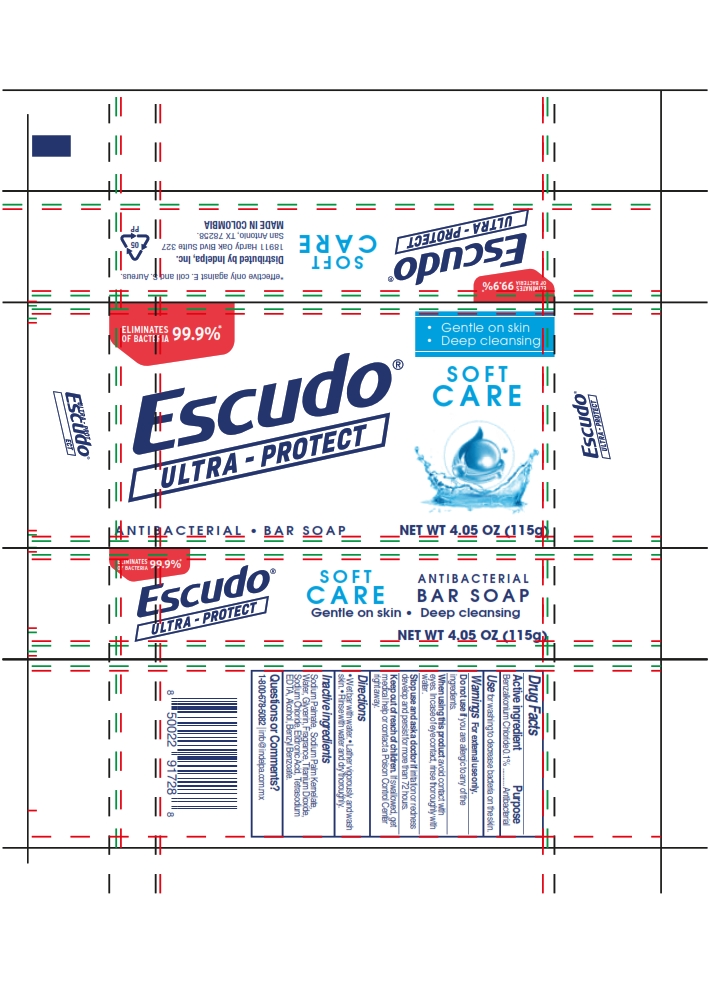 DRUG LABEL: Escudo Ultra-Protect Soft Care
NDC: 84529-002 | Form: SOAP
Manufacturer: Indelpa, Inc.
Category: otc | Type: HUMAN OTC DRUG LABEL
Date: 20260203

ACTIVE INGREDIENTS: BENZALKONIUM CHLORIDE 0.1 g/100 g
INACTIVE INGREDIENTS: SODIUM CHLORIDE; ETIDRONIC ACID; SODIUM PALMATE; GLYCERIN; TITANIUM DIOXIDE; FRAGRANCE 13576; WATER; ALCOHOL; BENZYL BENZOATE; SODIUM PALM KERNELATE; EDETATE SODIUM

Escudo Ultra-Protect Soft Care

Drug Facts

Active ingredient

Active ingredient------------------------- Purpose

Benzalkonium Chloride 0.1% .......... Antibacterial

Active ingredient -------------------------Purpose

Benzalkonium Chloride 0.1% .......... Antibacterial

Use

For washing to decrease bacteria on the skin.

Uses

for washing to decrease bacteria on the skin.

Warnings

For external use only.

Do not use if you are allergic to any of the ingredients.

When using this product avoid contact with eyes. In case of eye contact, rinse thoroughly with water.

Stop use and ask a doctor if irritation or redness develop and persist for more than 72 hours.

Keep out of reach of children. If swallowed, get medical help or contact a Poisn Center right away.

Directions

- Wet bar with water.
- Lather vigorously and wash skin.
- Rinse with water and dry throughly.

Inactive ingredients

Alcohol, Benzyl Benzoate, Etidronic Acid, Glycerin, Sodium Chloride, Sodium Kernelate, Sodium Palmate, Tetrasodium EDTA, Titanium Dioxide, Water, Fragrance.

Questions or Comments?

1-800-678-5082 I info@indelpa.com.mx

*effective only against E. coli and S. Aureus.

Distributed by Indelpa, Inc.

18911 Hardy Oak Blvd Suite 327

San Antonio, TX 78258.

MADE IN COLOMBIA

Package Label principal display panel

Eliminates 99.9%

of Bacteria

- Gentle on skin
- Deep cleansing

SOFT CARE

Escudo®

ULTRA-PROTECT

ANTIBACTERIAL BAR SOAP

NET WT 4.05 Z (115g)